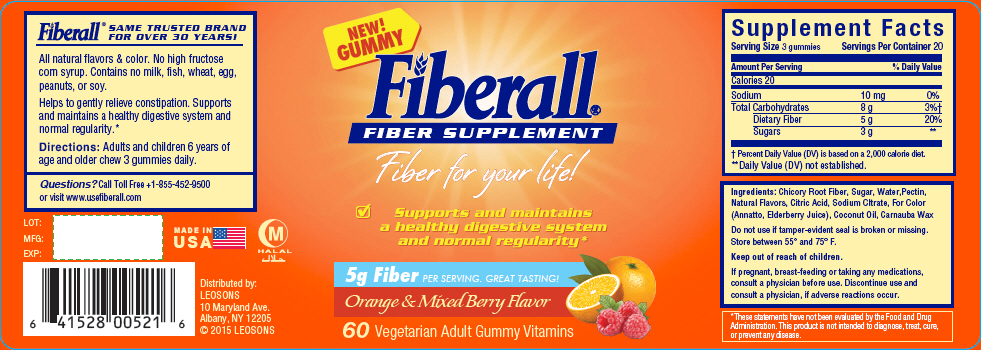 DRUG LABEL: Fiberall 
NDC: 69626-0521 | Form: TABLET, CHEWABLE
Manufacturer: Leosons Overseas Corp
Category: other | Type: DIETARY SUPPLEMENT
Date: 20180914

ACTIVE INGREDIENTS: Chicory Root 1.66 g/1 1
INACTIVE INGREDIENTS: Sucrose; Water; Pectin; Citric Acid Monohydrate; Sodium Citrate, Unspecified Form; Annatto; Coconut Oil; Carnauba Wax

Fiberall® FIBER SUPPLEMENT

STATEMENT OF IDENTITY

Supplement Facts
Serving Size 3 gummies | Servings Per Container 20
Amount Per Serving | % Daily Value
Calories 20
Sodium | 10 mg | 0%
Total Carbohydrates | 8 g | 3% [Percent Daily Value (DV) is based on a 2,000 calorie diet.]
Dietary Fiber | 5 g | 20%
Sugars | 3 g | [Daily Value (DV) not established.]

Ingredients: Chicory Root Fiber, Sugar, Water,Pectin, Natural Flavors, Citric Acid, Sodium CItrate, For Color (Annatto, Elderberry Juice), Coconut Oil, Carnauba Wax

Do not use if tamper-evident seal is broken or missing.

Store between 55° and 75° F.

Keep out of reach of children.

If pregnant, breast-feeding or taking any medications, consult a physician before use. Discontinue use and consult a physician, if adverse reactions occur.

HEALTH CLAIM

*These statements have not been evaluated by the Food and Drug Administration. This product is not intended to diagnose, treat, cure, or prevent any disease.

HEALTH CLAIM

Fiberall®
SAME TRUSTED BRAND FOR OVER 30 YEARS!

All natural flavors & color. No high fructose corn syrup. Contains no milk, fish, wheat, egg, peanuts, or soy.

Helps to gently relieve constipation. Supports and maintains a healthy digestive system and normal regularity.*

Directions

Adults and children 6 years of age and older chew 3 gummies daily.

Questions?

Call Toll Free +1-855-452-9500 or visit www.usefiberall.com

HEALTH CLAIM

LOT:

MFG:

EXP:

MADE IN USA

HALAL

Distributed by:
LEOSONS
10 Maryland Ave.
Albany, NY 12205
© 2015 LEOSONS

PRINCIPAL DISPLAY PANEL - 60 Vitamin Bottle Label

NEW!
GUMMY

Fiberall®
FIBER SUPPLEMENT

Fiber for your life!

☑ Supports and maintains
  a healthy digestive system
  and normal regularity*

5g Fiber PER SERVING. GREAT TASTING!

Orange & Mixed Berry Flavor

60 Vegetarian Adult Gummy Vitamins